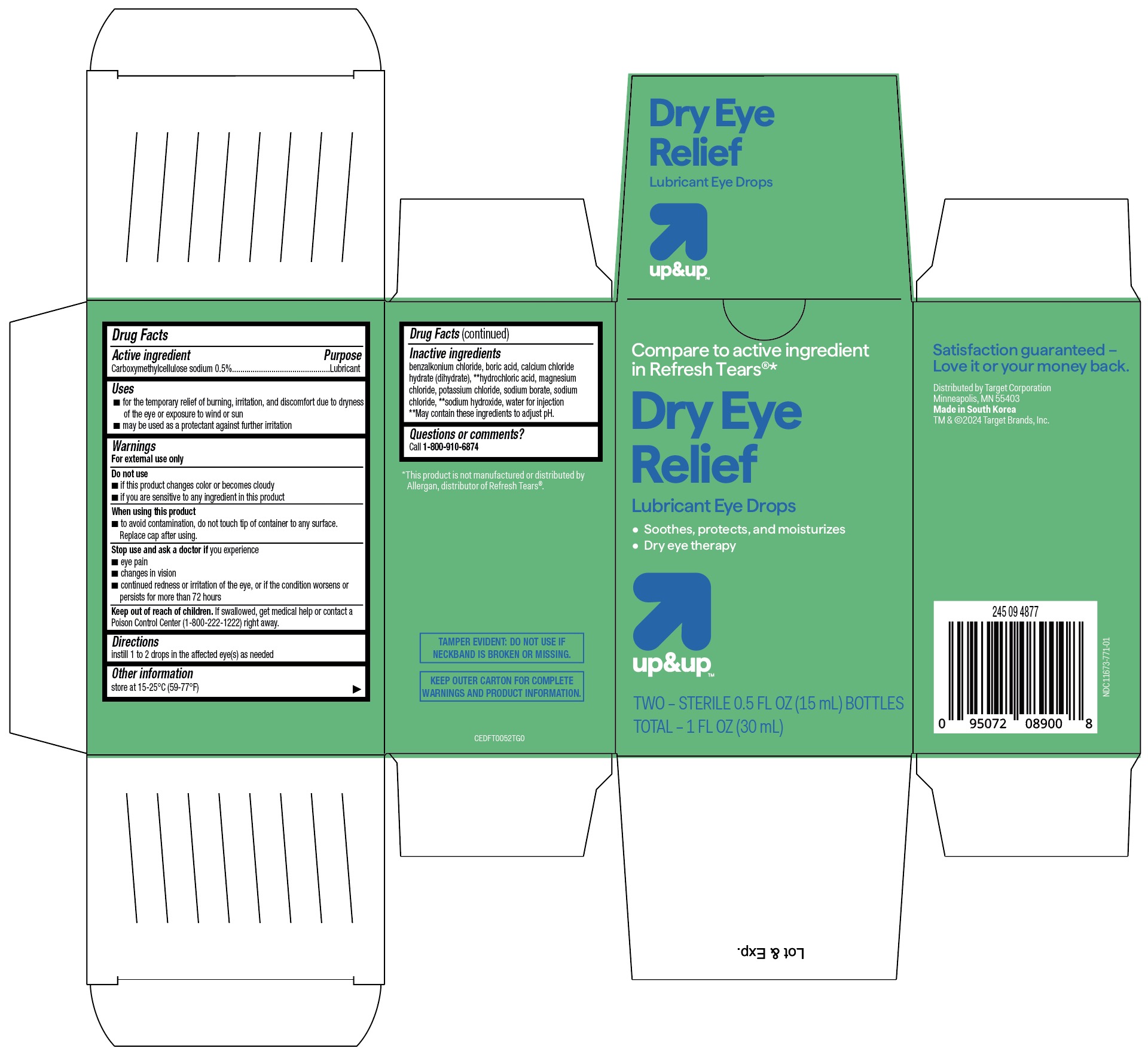 DRUG LABEL: Up and Up Dry Eye Relief Lubricant Eye Drops
NDC: 11673-771 | Form: SOLUTION/ DROPS
Manufacturer: Target Corporation
Category: otc | Type: HUMAN OTC DRUG LABEL
Date: 20251025

ACTIVE INGREDIENTS: CARBOXYMETHYLCELLULOSE SODIUM 5 mg/1 mL
INACTIVE INGREDIENTS: WATER; SODIUM CHLORIDE; CALCIUM CHLORIDE; POTASSIUM CHLORIDE; SODIUM HYDROXIDE; MAGNESIUM CHLORIDE; SODIUM BORATE; BORIC ACID; HYDROCHLORIC ACID; BENZALKONIUM CHLORIDE

Up & Up Dry Eye Relief Lubricant Eye Drops

Purpose.....Lubricant

KEEP OUT OF REACH OF CHILDREN

If swallowed, get medical help or contact a Poison Control Center immediately (1-800-222-1222) right away.

DOSAGE AND ADMINISTRATION

Instill 1 or 2 drops in the affected eye(s) as needed

ACTIVE INGREDIENT

Carboxymethylcellulose sodium 0.5%

INDICATIONS AND USAGE

- For the temporary relief of burning, irritation, and discomfort due to dryness of the eye or from irritation from wind or sun.
- May be used to protect against further irritation.

INACTIVE INGREDIENT

Inactive ingredients: benzalkonium chloride, boric acid, calcium chloride hydrate, hydrochloric acid, magnesium chloride, potassium chloride, sodium borate, sodium chloride, sodium hydroxide, water

WARNINGS

- For external use only.

DO NOT USE

- If solution changes color or becomes cloudy
- If you are sensitive or allergic to any ingredient in this product

WHEN USING

- To avoid contamination, do not touch tip of container to any surface.
- Replace cap after using.

STOP USE IF YOU

- Experience eye pain
- Have changes in vision occur redness
- Irritation of the eye(s) gets worse or lasts more than 72 hours